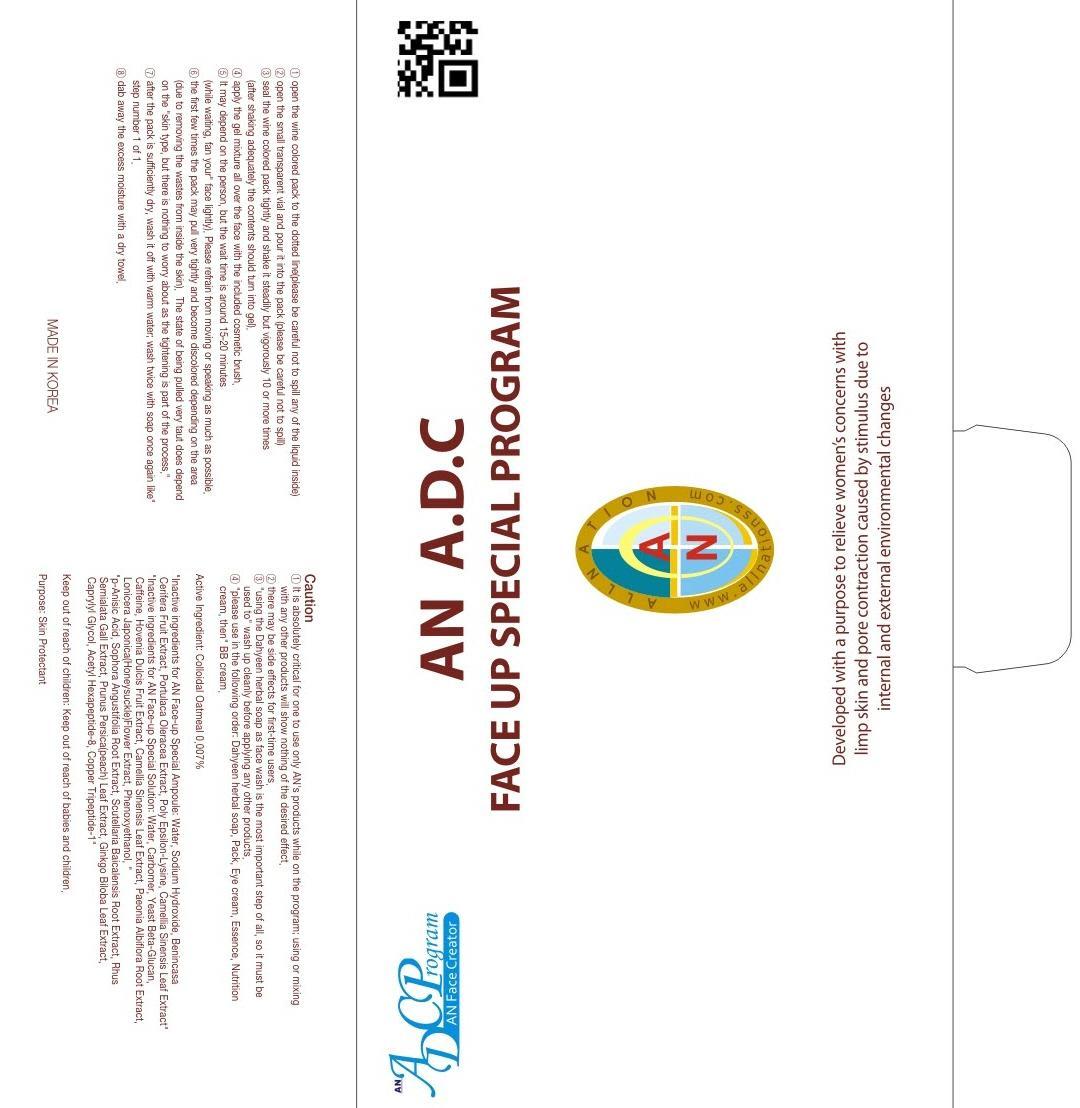 DRUG LABEL: AN ADC FACE UP SPECIAL PROGRAM
NDC: 69153-020 | Form: SOLUTION
Manufacturer: AN Co Ltd.
Category: otc | Type: HUMAN OTC DRUG LABEL
Date: 20140926

ACTIVE INGREDIENTS: OATMEAL 0.00007 mg/10 1
INACTIVE INGREDIENTS: Water; Caffeine

ACTIVE INGREDIENT

Active Ingredient: Colloidal Oatmeal 0.007%

INACTIVE INGREDIENT

Inactive ingredients for AN Face-up Special Ampoule: Water, Sodium Hydroxide, Benincasa Cerifera Fruit Extract, Portulaca Oleracea Extract, Poly Epsilon-Lysine, Camellia Sinensis Leaf Extract
Inactive ingredients for AN Face-up Special Solution: Water, Carbomer, Yeast Beta-Glucan, Caffeine, Hovenia Dulcis Fruit Extract, Camellia Sinensis Leaf Extract, Paeonia Albiflora Root Extract, Lonicera Japonica(Honeysuckle)Flower Extract, Phenoxyethanol,
p-Anisic Acid, Sophora Angustifolia Root Extract, Scutellaria Baicalensis Root Extract, Rhus Semialata Gall Extract, Prunus Persica(peach) Leaf Extract, Ginkgo Biloba Leaf Extract, Caprylyl Glycol, Acetyl Hexapeptide-8, Copper Tripeptide-1

PURPOSE

Purpose: Skin Protectant

Caution

1. It is absolutely critical for one to use only AN's products while on the program; using or mixing with any other products will show nothing of the desired effect.
2. There may be side effects for first-time users.
3. Using the Dahyeen herbal soap as face wash is the most important step of all, so it must be used to wash up cleanly before applying any other products.
4. Please use in the following order: Dahyeen herbal soap, Pack, Eye cream, Essence, Nutrition cream, then BB cream.

Keep out of reach of children: Keep out of reach of babies and children.

INDICATIONS & USAGE

1. Open the wine colored pack to the dotted line(please be careful not to spill any of the liquid inside)
2. Open the small transparent vial and pour it into the pack (please be careful not to spill)
3. Seal the wine colored pack tightly and shake it steadily but vigorously 10 or more times (after shaking adequately the contents should turn into gel).
4. Apply the gel mixture all over the face with the included cosmetic brush.
5. It may depend on the person, but the wait time is around 15-20 minutes (while waiting, fan your face lightly). Please refrain from moving or speaking as much as possible.
6. The first few times the pack may pull very tightly and become discolored depending on the area (due to removing the wastes from inside the skin). The state of being pulled very taut does depend on the skin type, but there is nothing to worry about as the tightening is part of the process.
7. After the pack is sufficiently dry, wash it off with warm water; wash twice with soap once again like step number 1 of 1.
8. Dab away the excess moisture with a dry towel.

DOSAGE & ADMINISTRATION

1. Open the wine colored pack to the dotted line(please be careful not to spill any of the liquid inside)
2. Open the small transparent vial and pour it into the pack (please be careful not to spill)
3. Seal the wine colored pack tightly and shake it steadily but vigorously 10 or more times (after shaking adequately the contents should turn into gel).
4. Apply the gel mixture all over the face with the included cosmetic brush.
5. It may depend on the person, but the wait time is around 15-20 minutes (while waiting, fan your face lightly). Please refrain from moving or speaking as much as possible.
6. The first few times the pack may pull very tightly and become discolored depending on the area (due to removing the wastes from inside the skin). The state of being pulled very taut does depend on the skin type, but there is nothing to worry about as the tightening is part of the process.
7. After the pack is sufficiently dry, wash it off with warm water; wash twice with soap once again like step number 1 of 1.
8. Dab away the excess moisture with a dry towel.